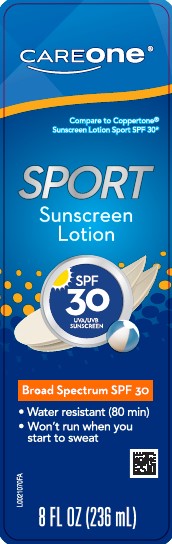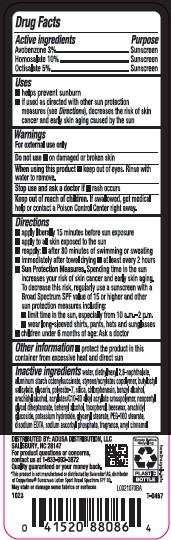 DRUG LABEL: Sport Sunscreen SPF 30
NDC: 72476-939 | Form: LOTION
Manufacturer: Retail Business Services, LLC
Category: otc | Type: HUMAN OTC DRUG LABEL
Date: 20260206

ACTIVE INGREDIENTS: AVOBENZONE 30 mg/1 mL; HOMOSALATE 100 mg/1 mL; OCTISALATE 50 mg/1 mL
INACTIVE INGREDIENTS: WATER; DIETHYLHEXYL 2,6-NAPHTHALATE; ALUMINUM STARCH OCTENYLSUCCINATE; STYRENE/ACRYLAMIDE COPOLYMER (500000 MW); BUTYLOCTYL SALICYLATE; GLYCERIN; POLYESTER-7; SILICON DIOXIDE; CHLORPHENESIN; BENZYL ALCOHOL; ARACHIDYL ALCOHOL; ACRYLATES/C10-30 ALKYL ACRYLATE CROSSPOLYMER (60000 MPA.S); NEOPENTYL GLYCOL DIHEPTANOATE; DOCOSANOL; TOCOPHEROL; YELLOW WAX; ARACHIDYL GLUCOSIDE; POTASSIUM HYDROXIDE; GLYCERYL MONOSTEARATE; PEG-100 STEARATE; EDETATE DISODIUM ANHYDROUS; SODIUM ASCORBYL PHOSPHATE; .ALPHA.-AMYLCINNAMALDEHYDE

Care One D39.000/D39AA
Sport Sunscreen Lotion SPF 30

Active ingredients

Avobenzone 3%

Homosalate 10%

Octisalate 5%

Purpose

Sunscreen

Uses

- helps prevent sunburn
- if used as directed with other sun protections measures (see Directions), decreases the risk of skin cancer and early skin aging caused by the sun

Warnings

For external use only

Do not use

- on damaged or broken skin

When using this product

- keep out of eyes. Rinse with water to remove.

Stop use and ask a doctor if

- rash occurs

Keep out of reach of children.

If swallowed, get medical help or contact a Poison Control Center right away.

Directions

- apply liberally 15 minutes before sun exposure
- apply to all skin exposed to the sun
- reapply:
- after 80 minutes of swimming or sweating
- immediately after towel drying
- at least every 2 hours
- Sun Protection Measures. Spending time in the sun increases your risk of skin cancer and early skin aging. To decrease this risk, regularly use a sunscreen with a Broad Spectrum SPF value of 15 or higher and other sun protection measures including:
- limit time in the sun, especially from 10 a.m.–2 p.m.
- wear long-sleeved shirts, pants, hats and sunglasses
- children under 6 months of age: Ask a doctor

Other information

- Protect the product in this container from excessive heat and direct sun

Inactive ingredients

water, diethylhexyl 2,6-naphthalate, aluminum starch octenylsuccinate, styrene/acrylates copolymer, butyloctyl salicylate, glycerin, polyester-7, silica, chlorphenesin, benzyl alcohol, arachidyl alcohol, acrylates/C10-30 alkyl acrylate crosspolymer, neopentyl glycol diheptanoate, behenyl alcohol, tocopherol, beeswax, arachidyl glucoside, potassium hydroxide, glyceryl stearate, PEG-100 stearate, disodium EDTA, sodium ascorbyl phosphate, fragrance, amyl cinnamal

Adverse reaction

DISTRIBUTED BY: ADUSA DISTRIBUTION, LLC

SALISBURY, NC 28147

For product questions or concerns, contact us at 1-833-992-3872

Quality guaranteed or your money back.

Empty Before Recycling

PLASTIC BOTTLE

how2recycle.info

Disclaimers

*This product is not manufactured or distributed by Beiersdorf AG, distributor of Coppertone® Sunscreen Lotion Sport Broad Spectrum SPF 30.

May stain or damage some fabrics or surfaces.

Principal display panel

CAREone®

Compare to Coppertone®Sunscreen Lotion Sport SPF 30*

SPORT

Sunscreen Lotion

SPF 30

UVA/UVB SUNCREEN

Broad Spectrum SPF 30

- Water resistant (80 min)
- Won't run when you start to sweat

8 FL OZ (236 mL)